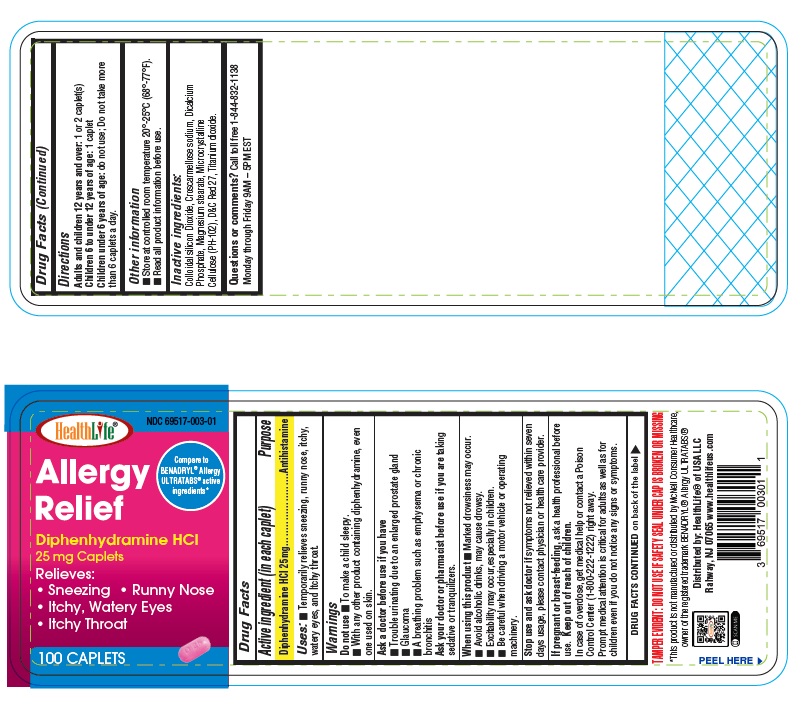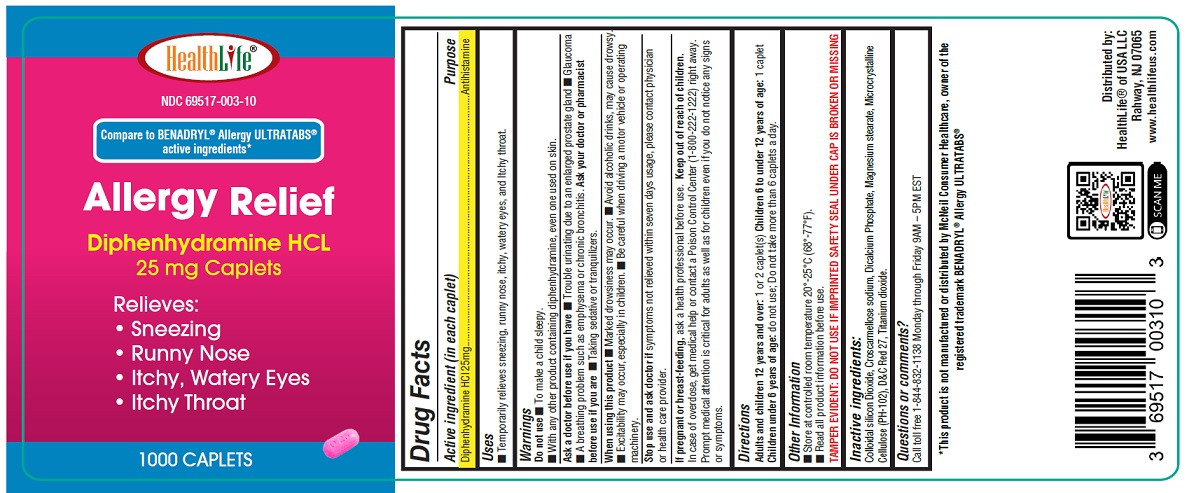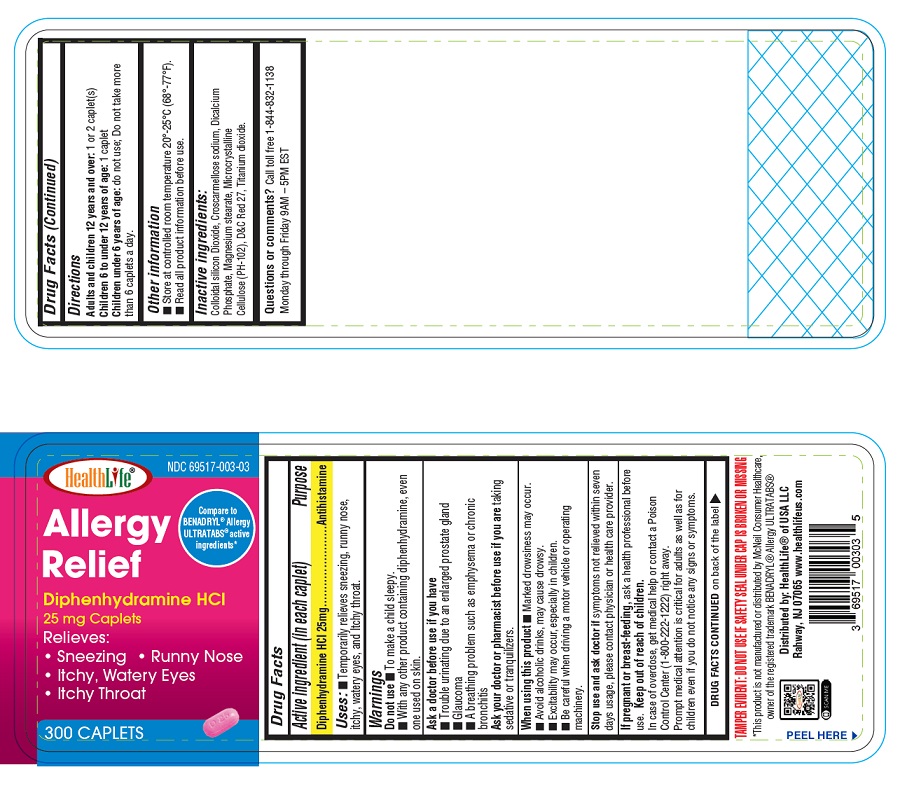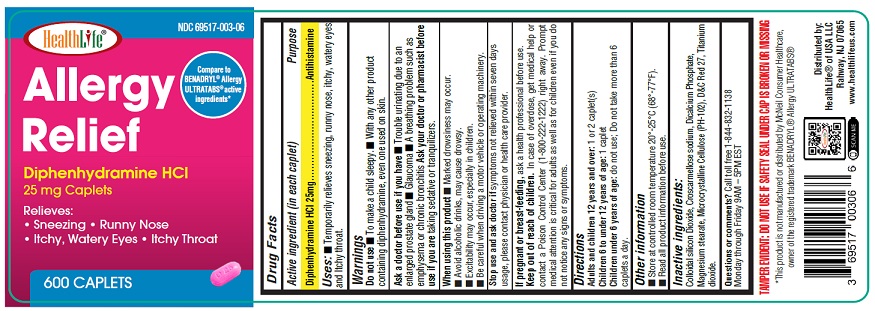 DRUG LABEL: Allergy Relief
NDC: 69517-003 | Form: TABLET
Manufacturer: HealthLife of USA LLC
Category: otc | Type: HUMAN OTC DRUG LABEL
Date: 20250917

ACTIVE INGREDIENTS: DIPHENHYDRAMINE HYDROCHLORIDE 25 mg/1 1
INACTIVE INGREDIENTS: ANHYDROUS DIBASIC CALCIUM PHOSPHATE; MICROCRYSTALLINE CELLULOSE; CROSCARMELLOSE SODIUM; SILICON DIOXIDE; MAGNESIUM STEARATE; D&C RED NO. 27; TITANIUM DIOXIDE

Active ingredient (in each caplet)

Diphenhydramine HCl 25 mg

Purpose

Antihistamine

Uses:

- Temporarily relieves Sneezing, runny nose, itchy, watery eyes, and itchy throat.

Do not use

- To make a child sleepy
- With any other product containing diphenhydramine, even one used on skin.

Ask a doctor before use if you have

- Trouble urinating due to an enlarged prostate gland
- Glaucoma
- A breathing problem such as emphysema or chronic bronchitis

Ask a doctor or pharmacist before use if you are

taking sedatives or tranquilizers.

When using this product

- Marked drowsiness may occur.
- Avoid alcoholic drinks, may cause drowsy.
- Excitability may occur, especially in children.
- Be careful when driving a motor vehicle or operating machinery.

Stop use and ask doctor if

symptoms not relieved within seven days usage, please contact physician or health care provider.

If pregnant or breast-feeding,

ask a health professional before use

Keep out of reach of children.

In case of accidental overdose, get medical help or contact a Poison Control Center (1-800-222-1222) right away. Prompt medical attention is critical for adults as well as for children even if you do not notice any signs or symptoms.

Directions

Adults and children 12 years and over:1 or 2 caplet (s)
Children 6 to under 12 years of age:1 caplet
Children under 6 years of age:do not use; Do not take more than 6 caplets a day.

Other Information

- Store at controlled room temperature 20°-25°C (68°-77°F).
- Read all product information before use.

Inactive Ingredients:

Colloidal silicon Dioxide, Croscarmellose sodium, Dicalcium Phosphate, Magnesium Stearate, Microcrystalline Cellulose (PH-102), D&C Red 27, Titanium dioxide.

Questions or comments?

Call toll free 1-844-832-1138

Monday through Friday 9AM- 5PM EST